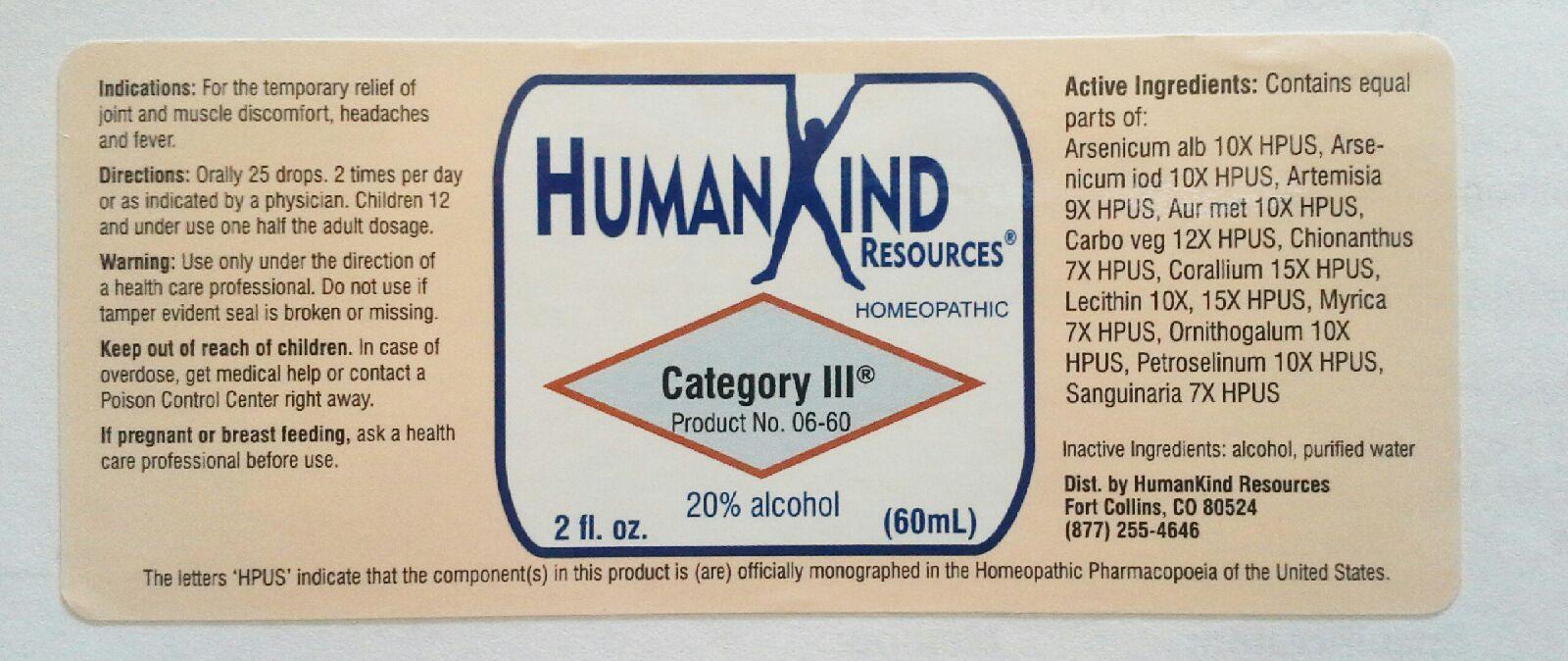 DRUG LABEL: Category III
NDC: 64616-084 | Form: LIQUID
Manufacturer: Vitality Works, Inc.
Category: homeopathic | Type: HUMAN OTC DRUG LABEL
Date: 20251217

ACTIVE INGREDIENTS: EGG PHOSPHOLIPIDS 15 [hp_X]/1 mL; MORELLA CERIFERA ROOT BARK 7 [hp_X]/1 mL; ORNITHOGALUM UMBELLATUM 10 [hp_X]/1 mL; PETROSELINUM CRISPUM 10 [hp_X]/1 mL; SANGUINARIA CANADENSIS ROOT 10 [hp_X]/1 mL; ARSENIC TRIOXIDE 10 [hp_X]/1 mL; ARSENIC TRIIODIDE 10 [hp_X]/1 mL; ARTEMISIA VULGARIS ROOT 9 [hp_X]/1 mL; GOLD 10 [hp_X]/1 mL; ACTIVATED CHARCOAL 12 [hp_X]/1 mL; CHIONANTHUS VIRGINICUS BARK 7 [hp_X]/1 mL; CORALLIUM RUBRUM EXOSKELETON 15 [hp_X]/1 mL
INACTIVE INGREDIENTS: ALCOHOL; WATER

Category III

Category III

Arsenicum Album 10X Corallium Rubrum 15X

Arsenicum Iodatum 8X Lecithin 10X

Artemisea Vulagaris 7X Myrica Cerifera 7X

Aurum Metallicum 10X Ornithogalum Umbellatum 10X

Carbo Vegetabilis 12X Pertoselinum Sativum 10X

Chionanthus Virginica 7X Sanguinaria Canadensis 7X

Category III

Alcohol, Purified Water

Category III

Use only under the direction of a health care professional. Do not use if tamper evident seal is broken or missing.

Category III

Kepp out of reach of children. In case of overdose, get medical help or contact a Poison Control Center right away.

Category III

For the temporary relief of headaches, malaise, fever, digestive upset and discomfort, sleeplessness and general unrest.

Category III

Orally 25 drops, per day or as indicated by a physician. Children 12 and under use one half the adult dosage.

Category III

Temporarely eases headaches, malaise, fever, digestive upset and discomfort, sleeplessness and general unrest.